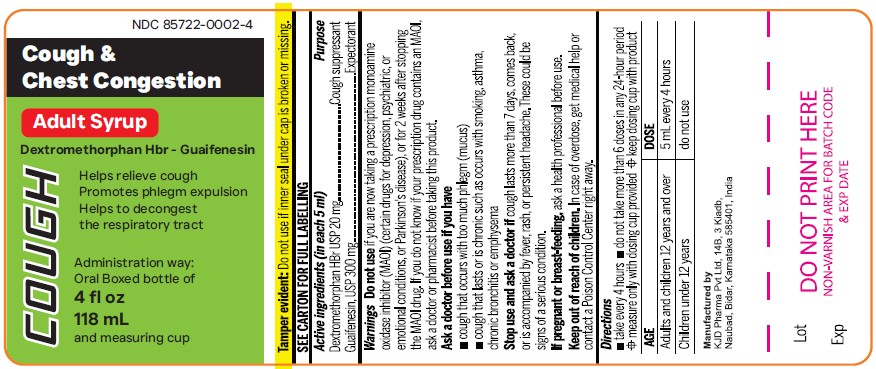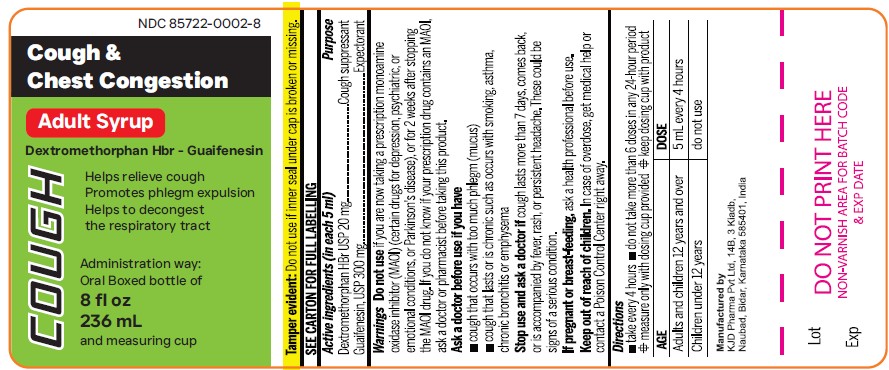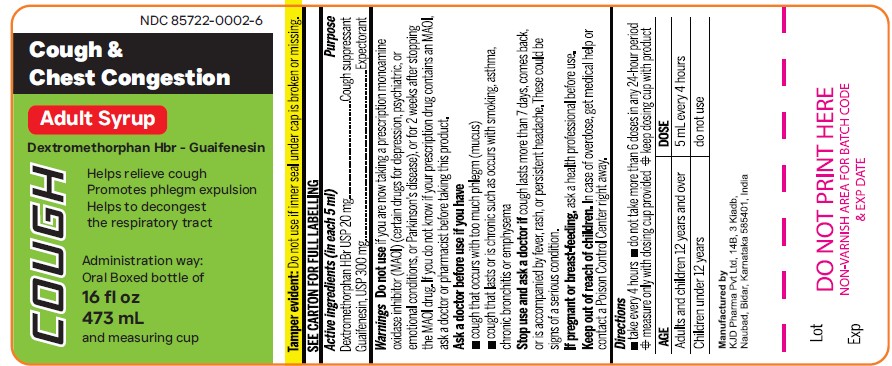 DRUG LABEL: DEXTROMETHORPHAN HYDROBROMIDE and GUAIFENESIN
NDC: 85722-0002 | Form: SYRUP
Manufacturer: KJD Pharma Private Limited
Category: otc | Type: HUMAN OTC DRUG LABEL
Date: 20250702

ACTIVE INGREDIENTS: DEXTROMETHORPHAN HYDROBROMIDE 20 mg/5 mL; GUAIFENESIN 300 mg/5 mL
INACTIVE INGREDIENTS: ANHYDROUS CITRIC ACID; GLYCERIN; MENTHOL; POLYETHYLENE GLYCOL, UNSPECIFIED; PROPYLENE GLYCOL; WATER; SODIUM BENZOATE; SACCHARIN SODIUM; SORBITOL

Cough & Chest CongestionDextromethorphan Hbr - Guaifenesin
ADULT Syrup 118 mL, 236 mL and 473 mL
and measuring cup

Active Ingredient (in each 5 mL) Purpose

Dextromethorphan HBr USP 20 mg............. Cough suppressant

Guaifenesin, USP 300 mg............................... Expectorant

PURPOSE

Relieves:
• Chest congestion / Mucus
• Cough

Uses

- temporarily relieves cough due to minor throat and bronchial irritation as may occur with a cold
- helps to loosen phlegm (mucus) and thin bronchial secretions to drain bronchial tubes

Warnings

DO NOT USE

- Do not useif you are now taking a prescription monoamine oxidase inhibitor (MAOI) (certain drugs for depression, psychiatric, or emotional conditions, or Parkinson's disease), or for 2 weeks after stopping the MAOI drug. If you do not know if your prescription drug contains an MAOI, ask a doctor or pharmacist before taking this product.

Ask a doctor before use if you have

- cough that occurs with too much phlegm (mucus)
- cough that lasts or is chronic such as occurs with smoking, asthma, chronic bronchitis or emphysema

Stop use and ask a doctor ifcough lasts more than 7 days, comes back, or is accompanied by fever, rash, or persistent headache. These could be signs of a serious condition.

KEEP OUT OF REACH OF CHILDREN

If pregnant or breast-feedingask a health professional before use.

Keep out of reach of children. In case of overdose, get medical help or contact a Poison Control Center right away.

Directions

- take evey 4 hours
- do not take more than 6 doses in any 24-hour period
- measure only with dosing cup provided
- keep dosing cup with product

Age | Dose
Adults and children 12 years and over | 5 mL every 4 hours
Children under 12 years | do not use

Other information

- Store at 20°-25°C (68° -77°F).
- Do not refrigerate.
- Retain carton for future reference on full labeling

Inactive ingredients

citric acid, flavor, glycerin, menthol, polyethylene glycol, propylene glycol, purified water, sodium benzoate, sodium saccharin, sorbitol.

Manufactured by
KJD Phanna Pvt lid, 148, 3 Kiadb,
Naubad, Bidar, Kamataka 585401 , India